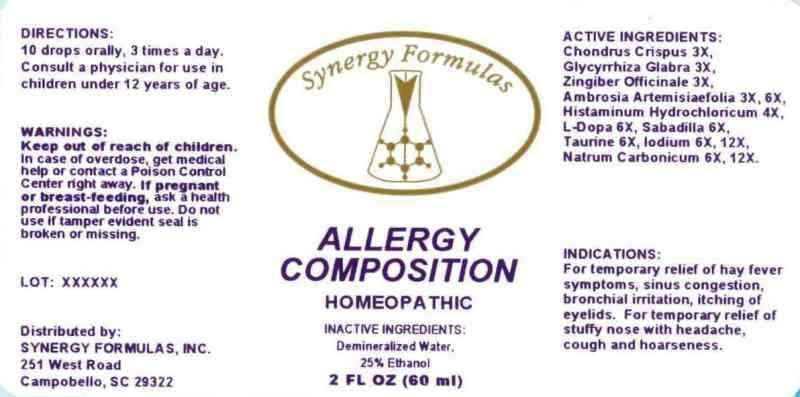 DRUG LABEL: Allergy Composition
NDC: 43772-0012 | Form: LIQUID
Manufacturer: Synergy Formulas, Inc.
Category: homeopathic | Type: HUMAN OTC DRUG LABEL
Date: 20130417

ACTIVE INGREDIENTS: CHONDRUS CRISPUS 3 [hp_X]/1 mL; GLYCYRRHIZA GLABRA 3 [hp_X]/1 mL; GINGER 3 [hp_X]/1 mL; AMBROSIA ARTEMISIIFOLIA 3 [hp_X]/1 mL; HISTAMINE DIHYDROCHLORIDE 4 [hp_X]/1 mL; ETILEVODOPA 6 [hp_X]/1 mL; SCHOENOCAULON OFFICINALE SEED 6 [hp_X]/1 mL; TAURINE 6 [hp_X]/1 mL; IODINE 6 [hp_X]/1 mL; SODIUM CARBONATE 6 [hp_X]/1 mL
INACTIVE INGREDIENTS: WATER; ALCOHOL

Drug Facts

ACTIVE INGREDIENTS

Chondrus Crispus 3X, Glycyrrhiza Glabra 3X, Zingiber Officinale 3X, Ambrosia Artemisiaefolia 3X, 6X, Histaminum Hydrochloricum 4X, L-Dopa 6X, Sabadilla 6X, Taurine 6X, Iodium 6X, 12X, Natrum Carbonicum 6X, 12X

INDICATIONS

For temporary relief of hay fever symptoms, sinus congestion, bronchial irritation, itching of eyelids. For temporary relief of stuffy nose with headache, cough and hoarseness.

WARNINGS

Keep out of reach of children. In case of overdose, get medical help or contact a Poison Control Center right away. If pregnant or breast-feeding, ask a health professional before use. Do not use if tamper evident seal is broken or missing.

DIRECTIONS

10 drops orally, 3 times a day. Consult a physician for use in children under 12 years of age.

INACTIVE INGREDIENTS

Demineralized water, 25% Ethanol.

KEEP OUT OF REACH OF CHILDREN

In case of overdose, get medical help or contact a Poison Control Center right away.

INDICATIONS AND USAGE

For temporary relief of hay fever symptoms, sinus congestion, bronchial irritation, itching of eyelids. For temporary relief of stuffy nose with headache, cough and hoarseness.

QUESTIONS

Distributed by:

SYNERGY FORMULAS, INC.

251 West Road

Campobello, SC 29322

PACKAGE LABEL

Synergy Formulas

ALLERGY COMPOSITION

HOMEOPATHIC

2 FL OZ (60 ml)